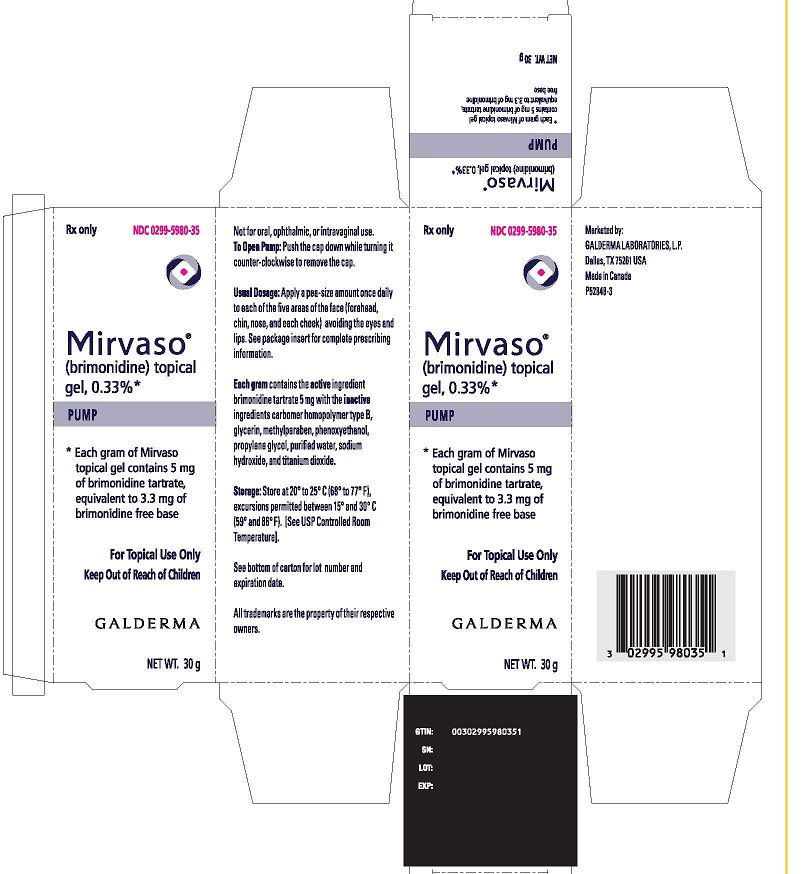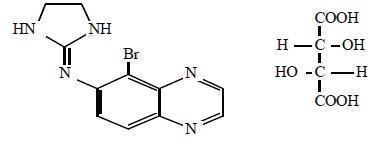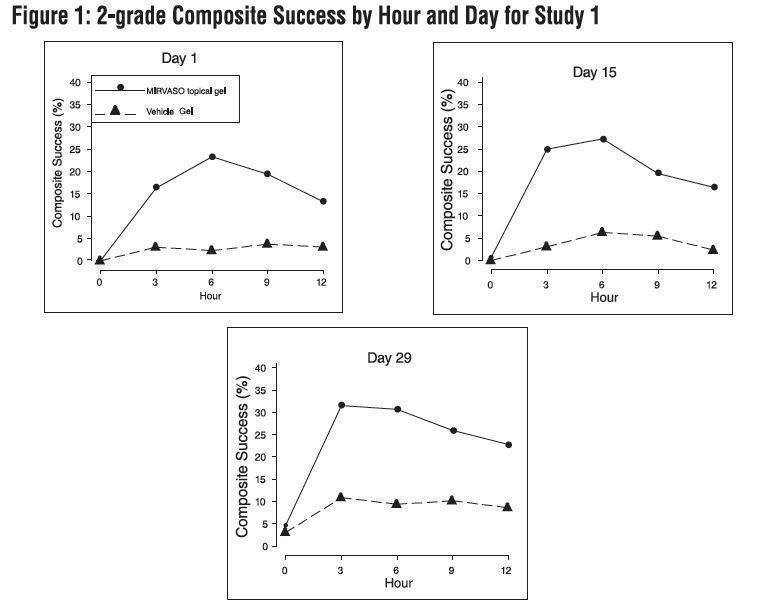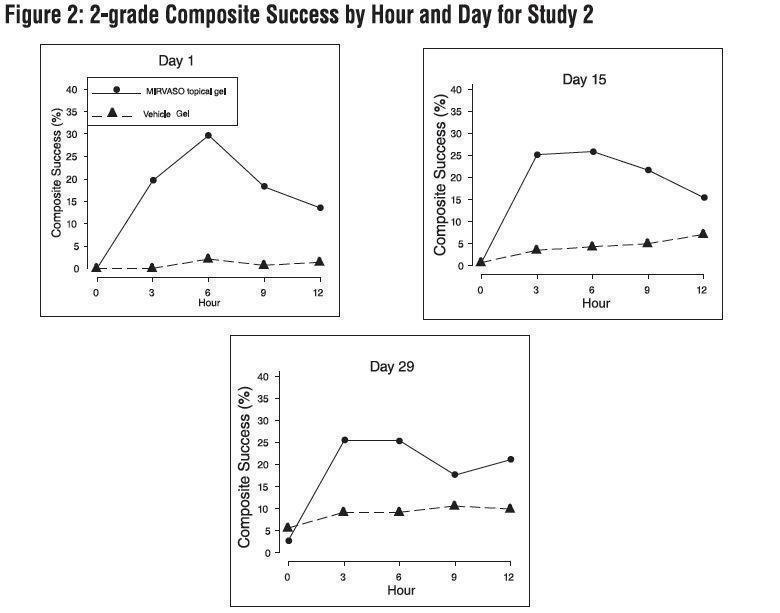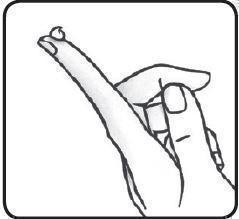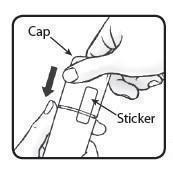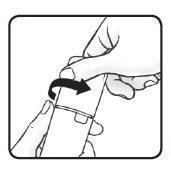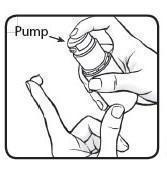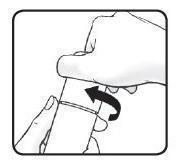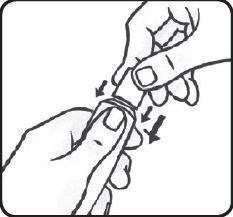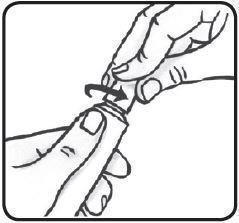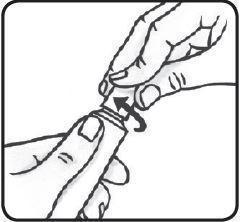 DRUG LABEL: Mirvaso
NDC: 0299-5980 | Form: GEL
Manufacturer: Galderma Laboratories, L.P.
Category: prescription | Type: HUMAN PRESCRIPTION DRUG LABEL
Date: 20241024

ACTIVE INGREDIENTS: BRIMONIDINE TARTRATE 5 mg/1 g
INACTIVE INGREDIENTS: CARBOMER HOMOPOLYMER TYPE B (ALLYL PENTAERYTHRITOL CROSSLINKED); GLYCERIN; METHYLPARABEN; PHENOXYETHANOL; PROPYLENE GLYCOL; WATER; SODIUM HYDROXIDE; TITANIUM DIOXIDE

HIGHLIGHTS OF PRESCRIBING INFORMATION

These highlights do not include all the information needed to use MIRVASO®safely and effectively. See full prescribing information for MIRVASO.
MIRVASO (brimonidine) topical gel
Initial U.S. Approval: 1996

RECENT MAJOR CHANGES

- Contraindications (4) 07/2016
- Warnings and Precautions (5.4, 5.5, 5.6) 07/2016

1 INDICATIONS AND USAGE

MIRVASO (brimonidine) topical gel, 0.33% is an alpha adrenergic agonist indicated for the topical treatment of persistent (nontransient) facial erythema of rosacea in adults 18 years of age or older.(1)

2 DOSAGE AND ADMINISTRATION

- Apply a pea-sized amount once daily to each of the five areas of the face (forehead, chin, nose, each cheek) avoiding the eyes and lips. (2)
- Hands should be washed immediately after applying MIRVASO topical gel. (2)
- For topical use only (2)
- Not for oral, ophthalmic, or intravaginal use. (2)

3 DOSAGE FORMS AND STRENGTHS

Gel, 0.33%; Each gram of gel contains 5 mg of brimonidine tartrate, equivalent to 3.3 mg of brimonidine free base. (3)

4 CONTRAINDICATIONS

Known hypersensitivity to any component of MIRVASO topical gel (4)

5 WARNINGS AND PRECAUTIONS

- Potentiation of Vascular Insufficiency (5.1)
- Severe Cardiovascular Disease (5.2)
- Serious Adverse Reactions Following Ingestion of MIRVASO topical gel (5.3)
- Systemic Adverse Reactions of Alpha-2 Adrenergic Agonists (5.4)
- Local Vasomotor Adverse Reactions (5.5)
- Hypersensitivity (5.6)

6 ADVERSE REACTIONS

In controlled clinical trials with MIRVASO topical gel the most common adverse reactions (incidence >1%) included erythema, flushing, skin burning sensation, and contact dermatitis. (6)
To report SUSPECTED ADVERSE REACTIONS, contact Galderma Laboratories, L.P. at 1-866-735-4137 or FDA at 1-800-FDA-1088 or www.fda.gov/medwatch.

FULL PRESCRIBING INFORMATION

1 INDICATIONS AND USAGE

MIRVASO (brimonidine) topical gel, 0.33% is an alpha adrenergic agonist indicated for the topical treatment of persistent (nontransient) erythema of rosacea in adults 18 years of age or older.

2 DOSAGE AND ADMINISTRATION

Apply a pea-sized amount once daily to each of the five areas of the face: central forehead, chin, nose, each cheek. MIRVASO topical gel should be applied smoothly and evenly as a thin layer across the entire face avoiding the eyes and lips.

Wash hands after applying MIRVASO topical gel.

MIRVASO topical gel is for topical use only and not for oral, ophthalmic, or intravaginal use.

3 DOSAGE FORMS AND STRENGTHS

MIRVASO (brimonidine) topical gel, 0.33% is a white to light yellow opaque aqueous gel. Each gram of gel contains 5 mg of brimonidine tartrate, equivalent to 3.3 mg of brimonidine free base.

4 CONTRAINDICATIONS

MIRVASO topical gel is contratindicated in patients who have experienced a hypersensitivity reaction to any component. Reactions have included angioedema, urticaria, and contact dermatitis [ see Warnings and Precautions (5.6)and Adverse Reactions (6.1, 6.2) ].

5 WARNINGS AND PRECAUTIONS

5.1 Potentiation of Vascular Insufficiency

MIRVASO topical gel should be used with caution in patients with depression, cerebral or coronary insufficiency, Raynaud’s phenomenon, orthostatic hypotension, thrombangiitis obliterans, scleroderma, or Sjögren’s syndrome.

5.2 Severe Cardiovascular Disease

Alpha-2 adrenergic agonists can lower blood pressure. MIRVASO topical gel should be used with caution in patients with severe or unstable or uncontrolled cardiovascular disease.

5.3 Serious Adverse Reactions Following Ingestion of MIRVASO topical gel

Two young children of a subject in a clinical trial experienced serious adverse reactions following accidental ingestion of MIRVASO topical gel. Adverse reactions experienced by one or both children included lethargy, respiratory distress with apneic episodes (requiring intubation), sinus bradycardia, confusion, psychomotor hyperactivity, and diaphoresis. Both children were hospitalized overnight and discharged the following day without sequelae.

Keep MIRVASO topical gel out of the reach of children.

5.4 Systemic Adverse Reactions of Alpha-2 Adrenergic Agonists

Postmarketing cases of bradycardia, hypotension (including orthostatic hypotension) and dizziness have been reported. Some cases required hospitalization. Some cases involved application of MIRVASO topical gel in unapproved dosing regimens and for unapproved indications, including the application of MIRVASO topical gel following laser procedures.

Avoid applying MIRVASO topical gel to irritated skin or open wounds.

5.5 Local Vasomotor Adverse Reactions

Erythema

Some subjects in the clinical trials discontinued use of MIRVASO topical gel because of erythema. Some subjects in the clinical trials reported a rebound phenomenon, where erythema was reported to return worse compared to the severity at baseline.

Erythema appeared to resolve after discontinuation of MIRVASO topical gel .[see Adverse Reactions (6.1)].

The treatment effect of MIRVASO topical gel may begin to diminish hours after application.

From postmarketing reports, some patients have experienced erythema involving areas of the face that were previously not affected by erythema and in areas (e.g., neck and chest) outside of the treatment sites.

Flushing

Some subjects in the clinical trials discontinued use of MIRVASO topical gel because of flushing.

Intermittent flushing occurred in some subjects treated with MIRVASO topical gel in the clinical trials. The onset of flushing relative to application of MIRVASO topical gel varied, ranging from approximately 30 minutes to several hours [ see Adverse Reactions (6.1) ]. Flushing appeared to resolve after discontinuation of MIRVASO topical gel.

From postmarketing reports, some patients have experienced increased frequency of flushing and/or increased depth of

erythema with the flushing. Additionally, some patients reported new onset of flushing.

Pallor and Excessive Whitening

From postmarketing reports, some patients have experienced pallor or excessive whitening at or outside the application site following treatment with MIRVASO topical gel.

5.6 Hypersensitivity

Allergic contact dermatitis was reported in the clinical trials for MIRVASO topical gel [ see Adverse Reactions (6.1) ].

Events reported post marketing with the use of MIRVASO topical gel include angioedema, throat tightening, tongue swelling, and urticaria, [ see Adverse Reactions (6.2) ]. Institute appropriate therapy and discontinue MIRVASO topical gel, if clinically significant hypersensitivity reaction occurs.

6 ADVERSE REACTIONS

The following adverse drug reactions are discussed in greater detail in other sections of the label:

- Systemic Adverse Reactions of Alpha-2 Adrenergic Agonists [ see Warnings and Precautions (5.4) ]
- Local Vasomotor Adverse Reactions [ see Warnings and Precautions (5.5) ]
- Hypersensitivity [ see Warnings and Precautions (5.6) ]

6.1 Clinical Trials Experience

Because clinical trials are conducted under widely varying conditions, adverse reaction rates observed in the clinical trials of a drug cannot be directly compared to rates in the clinical trials of another drug and may not reflect the rates observed in practice.

During clinical trials, 1210 subjects were exposed to MIRVASO topical gel. A total of 833 subjects were treated for persistent (nontransient) erythema associated with rosacea, and 330 of those were treated once daily for 29 days in vehicle-controlled trials.

Adverse reactions that occurred in at least 1% of subjects treated with MIRVASO topical gel once daily for 29 days and for which the rate for MIRVASO topical gel exceeded the rate for vehicle are presented in Table 1.

Table 1 - Adverse Reactions Reported in Clinical Trials by at Least 1% of Subjects Treated for 29 Days
Preferred Term | MIRVASO Topical Gel (N=330) n (%) | Vehicle Gel (N=331) n (%)
Subjects with at least one adverse reaction, Number (%) of Subjects | 109 (33) | 91 (28)
Erythema | 12 (4%) | 3 (1%)
Flushing | 9 (3%) | 0
Skin burning sensation | 5 (2%) | 2 (1%)
Dermatitis contact | 3 (1%) | 1 (<1%)
Dermatitis | 3 (1%) | 1 (<1%)
Skin warm | 3 (1%) | 0
Paraesthesia | 2 (1%) | 1 (<1%)
Acne | 2 (1%) | 1 (<1%)
Pain of skin | 2 (1%) | 0
Vision blurred | 2 (1%) | 0
Nasal congestion | 2 (1%) | 0

Open-label, Long-term Study
An open-label study of MIRVASO topical gel when applied once daily for up to one year was conducted in subjects with persistent (nontransient) facial erythema of rosacea. Subjects were allowed to use other rosacea therapies. A total of 276 subjects applied MIRVASO topical gel for at least one year. The most common adverse events (>4% of subjects) for the entire study were flushing (10%), erythema (8%), rosacea (5%), nasopharyngitis (5%), skin burning sensation (4%), increased intraocular pressure (4%), and headache (4%).

Allergic contact dermatitis
Allergic contact dermatitis to MIRVASO topical gel was reported in approximately 1% of subjects across the clinical development program. Two subjects underwent patch testing with individual product ingredients. One subject was found to be sensitive to brimonidine tartrate, and one subject was sensitive to phenoxyethanol (a preservative).

6.2 Postmarketing Experience

The following adverse reactions have been identified during post-approval use of MIRVASO topical gel. Because these reactions are reported voluntarily from a population of uncertain size, it is not always possible to estimate their frequency or establish a causal relationship to drug exposure.

Cardiovascular disorders:bradycardia, hypotension (including orthostatic hypotension)

Immune system disorders:angioedema, hypersensitivity, lip swelling, swollen tongue, throat tightness, urticaria

Nervous systemic disorders:dizziness

Skin and subcutaneous disorders:pallor

7 DRUG INTERACTIONS

7.1 Anti-hypertensives/Cardiac Glycosides

Alpha-2 agonists, as a class, may reduce blood pressure. Caution in using drugs such as beta-blockers, anti-hypertensives and/or cardiac glycosides is advised.

7.2 CNS Depressants

Although specific drug-drug interactions studies have not been conducted with MIRVASO topical gel, the possibility of an additive or potentiating effect with CNS depressants (alcohol, barbiturates, opiates, sedatives, or anaesthetics) should be considered.

7.3 Monoamine Oxidase Inhibitors

Monoamine oxidase (MAO) inhibitors may theoretically interfere with the metabolism of brimonidine and potentially result in an increased systemic side-effect such as hypotension. Caution is advised in patients taking MAO inhibitors which can affect the metabolism and uptake of circulating amines.

8 USE IN SPECIFIC POPULATIONS

8.1 Pregnancy

Pregnancy Category B.

There are no adequate and well-controlled studies of MIRVASO topical gel in pregnant women. In animal studies, brimonidine crossed the placenta and entered into the fetal circulation to a limited extent. MIRVASO topical gel should be used during pregnancy only if the potential benefit justifies the potential risk to the fetus.

Brimonidine tartrate was not teratogenic when given at oral doses up to 2.5 mg/kg/day in pregnant rats during gestation days 6 through 15 and 5 mg/kg/day in pregnant rabbits during gestation days 6 through 18.

8.3 Nursing Mothers

It is not known whether brimonidine tartrate is excreted in human milk, although in animal studies, brimonidine tartrate has been shown to be excreted in breast milk. Because of the potential for serious adverse reactions from MIRVASO topical gel in nursing infants, a decision should be made whether to discontinue nursing or to discontinue the drug, taking into account the importance of the drug to the mother.

8.4 Pediatric Use

Keep MIRVASO topical gel out of reach of children. Serious adverse reactions were experienced by two children of a subject in a clinical trial who accidentally ingested MIRVASO topical gel [See Warnings and Precautions (5.3) ].

Safety and effectiveness in pediatric patients have not been established.

8.5 Geriatric Use

One hundred and five subjects aged 65 and older were included in clinical trials with MIRVASO topical gel. No overall differences in safety or effectiveness were observed between subjects >65 years of age and younger adult subjects. Clinical studies of MIRVASO topical gel did not include sufficient numbers of subjects aged 65 and over to determine whether they respond differently from younger subjects.

10 OVERDOSAGE

No information is available on overdose in adults with MIRVASO topical gel.

Oral overdoses of other alpha-2 adrenergic agonists have been reported to cause symptoms such as hypotension, asthenia, vomiting, lethargy, sedation, bradycardia, arrhythmias, miosis, apnoea, hypotonia, hypothermia, respiratory depression, and seizure.

Treatment of an oral overdose includes supportive and symptomatic therapy; a patent airway should be maintained.

11 DESCRIPTION

MIRVASO (brimonidine) topical gel, 0.33% contains brimonidine tartrate, an alpha adrenergic agonist.

The molecular formula of brimonidine tartrate is C11H10BrN5• C4H6O6. It has the following structural formula:

Chemically, brimonidine tartrate is 5-Bromo-6-(2-imidazolidinylideneamino) quinoxaline L-tartrate. Brimonidine tartrate has a molecular weight of 442.24 and appears as white to slightly yellowish powder.

Each gram of MIRVASO (brimonidine) topical gel, 0.33% contains 5 mg of the active ingredient brimonidine tartrate (equivalent to 3.3 mg of brimonidine free base), in a white to light yellow opaque gel composed of the inactive ingredients carbomer homopolymer type B, glycerin, methylparaben, phenoxyethanol, propylene glycol, purified water, sodium hydroxide, and titanium dioxide.

12 CLINICAL PHARMACOLOGY

12.1 Mechanism of Action

Brimonidine is a relatively selective alpha-2 adrenergic agonist. Topical application of MIRVASO topical gel may reduce erythema through direct vasoconstriction.

12.3 Pharmacokinetics

Absorption

The absorption of brimonidine from MIRVASO topical gel was evaluated in a clinical trial in 24 adult subjects with facial erythema associated with rosacea. All enrolled subjects received once daily topical application of MIRVASO topical gel 1 gram to the entire face for 29 days. Pharmacokinetic assessments were performed on Day 1, Day 15, and Day 29. The mean plasma maximum concentration (Cmax) and area under the concentration-time curve (AUC) were highest on Day 15, with Cmaxand AUC values (± standard deviation) of 46 ± 62 pg/mL and 417 ± 264 pg.hr/mL, respectively. The systemic drug exposure was slightly lower on Day 29 indicating no further drug accumulation.

Metabolism

Brimonidine is extensively metabolized by the liver.

Excretion

Urinary excretion is the major route of elimination of brimonidine and its metabolites.

13 NONCLINICAL TOXICOLOGY

13.1 Carcinogenesis, Mutagenesis, Impairment of Fertility

Carcinogenesis

In a 21-month oral (diet) mouse carcinogenicity study and a 24-month oral (diet) rat carcinogenicity study, no drug-related neoplasms were observed in mice at oral doses of brimonidine tartrate up to 2.5 mg/kg/day or in rats at oral doses of brimonidine tartrate up to 1 mg/kg/day.

In a dermal rat carcinogenicity study with MIRVASO topical gel, brimonidine tartrate was administered to Wistar rats at topical doses of 0.9 (0.03% gel), 1.8 (0.06% gel), and 5.4 mg/kg/day (0.18% gel) in males and 5.4 (0.18% gel), 30 (1% gel) during Days 1-343/10.8 (0.36% gel) thereafter, and 60 (2% gel) during Days 1-343/21.6 mg/kg/day (0.72% gel) thereafter in females once daily for 24 months. No drug-related neoplasms were observed in this study.

In a 12-month dermal photo-carcinogenicity study, topical doses of 0% (MIRVASO topical gel vehicle), 0.18%, 1% and 2% brimonidine tartrate gel were administered to hairless albino mice once daily, five days per week, with concurrent exposure to simulated sunlight. No drug-related adverse effects were observed in this study. The results of this study suggest that topical treatment with MIRVASO topical gel would not enhance photo-carcinogenesis.

Mutagenesis

Brimonidine tartrate was not mutagenic or clastogenic in a series of in vitroand in vivostudies, including the Ames test, a chromosomal aberration assay in Chinese Hamster Ovary (CHO) cells, and three studies in CD1 mice (a host-mediated assay, a cytogenetic study, and a dominant lethal assay).

Impairment of Fertility

Reproduction and fertility studies in rats with brimonidine tartrate demonstrated no adverse effects on male or female fertility at oral doses up to 1 mg/kg/day.

14 CLINICAL STUDIES

MIRVASO topical gel was evaluated for the treatment of moderate to severe, persistent (nontransient) facial erythema of rosacea in two randomized, double-blind, vehicle-controlled clinical trials, which were identical in design. The trials were conducted in 553 subjects aged 18 years and older who were treated once daily for 4 weeks with either MIRVASO topical gel or vehicle. Overall, 99% of subjects were Caucasian and 76% were female. Baseline disease severity was graded using a 5-point Clinical Erythema Assessment (CEA) scale and a 5-point Patient Self Assessment (PSA) scale, on which subjects scored either “moderate” or “severe” on both scales.

The primary efficacy endpoint in both pivotal trials was 2-grade Composite Success, defined as the proportion of subjects with a 2-grade improvement on both CEA and PSA measured at hours 3, 6, 9, and 12 on Day 29. Table 2 presents the efficacy results. In addition to Day 29, efficacy was evaluated on Day 15 and Day 1, and the results are presented in Figures 1 and 2 for Studies 1 and 2, respectively.

Table 2: Summary of 2-grade Composite Success on Day 29
Success | Study 1 |  | Study 2
 | MIRVASO Topical Gel (N=129) | Vehicle Gel (N=131) | MIRVAO Topical Gel (N=148) | Vehicle Gel (N=145)
Hour 3 | 31% | 11% | 25% | 9%
Hour 6 | 30% | 10% | 25% | 9%
Hour 9 | 26% | 10% | 18% | 11%
Hour 12 | 23% | 9% | 22% | 10%

2-grade Composite Success: 2-grade improvement on CEA and 2-grade improvement on PSA.

16 HOW SUPPLIED/STORAGE AND HANDLING

MIRVASO (brimonidine) topical gel, 0.33% is a white to light yellow opaque gel, supplied in a laminated tube or pump with a child resistant cap in the following sizes:

30 gram tube NDC0299-5980-30

30 gram pump NDC0299-5980-35

45 gram tube NDC0299-5980-45

Store at 20°C to 25°C (68°F to 77°F), excursions permitted between 15°C and 30°C (59°F and 86°F) [See USP Controlled Room Temperature].

17 PATIENT COUNSELING INFORMATION

See FDA-approved patient labeling (Patient Information and Instructions for Use)

Patients using MIRVASO topical gel should receive the following information and instructions:

- This medication is to be used as directed by the physician.
- It is for external use only.
- MIRVASO topical gel should not be applied to irritated skin or open wounds.
- Avoid contact with the eyes and lips.
- Patients should wash their hands immediately after applying the medication.
- Some patients using MIRVASO topical gel may experience erythema, flushing or excessive whitening.
- Patients should report any adverse reactions to their physician.
- Keep out of reach of children.

Marketed by:

GALDERMA LABORATORIES, L.P., Fort Worth, Texas 76177 USA

Made in Canada.

All trademarks are the property of their respective owners.

P52849-2 or P51217-3

PATIENT INFORMATION

MIRVASO (Mer-VAY-soe)
(brimonidine)
topical gel

Important information:MIRVASO®topical gel is for use on the face only. Do not use MIRVASO topical gel in your eyes, mouth, or vagina.
Keep MIRVASO topical gel out of the reach of children.
If anyone, especially a child, accidentally swallows MIRVASO topical gel, they may have serious side effects and need to be treated in a hospital. Get medical help right away if you, a child, or anyone else swallows MIRVASO topical gel and has any of these symptoms:
• lack of energy, trouble breathing or stops breathing, a slow heart beat, confusion, sweating, restlessness, muscle spasms, or twitching.

What is MIRVASO topical gel?
MIRVASO topical gel is a prescription medicine that is used on your skin (topical) to treat facial redness due to rosacea that does not go away (persistent) in adults who are 18 years of age or older.

It is not known if MIRVASO topical gel is safe and effective in children.

Who should not use MIRVASO topical gel?

Do not use MIRVASO topical gel if youhave had a serious allergic reaction to any of the ingredients in MIRVASO topical gel. See the end of this Patient Information leaflet for a list of ingredients in MIRVASO topical gel. See “What are the possible side effects of MIRVASO topical gel?”

What should I tell my doctor before using MIRVASO topical gel?
Before using MIRVASO topical gel, tell your doctor about all of your medical conditions including if you:

• have depression
• have heart or blood vessel problems
• have dizziness or blood pressure problems
• have problems with blood circulation or have had a stroke
• have dry mouth or Sjögren’s Syndrome
• have skin tightening or scleroderma
• have Raynaud’s phenomenon
• have irritated skin or open sores
• plan to have any laser procedures
• are pregnant or plan to become pregnant. It is not known if MIRVASO topical gel will harm your unborn baby.
• are breastfeeding. It is not known if MIRVASO topical gel passes into your breast milk. You and your doctor should decide if you will use MIRVASO topical gel or breastfeed. You should not do both.

Tell your doctor about all the medicines you take, including prescription and over-the-counter medicines, skin products, vitamins, and herbal supplements. Using MIRVASO topical gel with certain other medicines may affect each other and can cause serious side effects.

How should I use MIRVASO topical gel?

See the detailed Instructions for Use that comes with your MIRVASO topical gel tube or pump for information about how to apply MIRVASO topical gel correctly.

• Use MIRVASO topical gel exactly as your doctor tells you.Do not use more MIRVASO topical gel than prescribed. Call your doctor if you are not sure.
• You should not apply MIRVASO topical gel to irritated skin or open wounds.
• MIRVASO topical gel is for use on your skin only. Do not use MIRVASO topical gel in your eyes, mouth, or vagina. Avoid contact with your lips and eyes.

What are the possible side effects of MIRVASO topical gel?

MIRVASO topical gel may cause serious side effects, including:

• See “Important information” at the beginning of this Patient Information leaflet.

• Problems with blood circulation.People who use MIRVASO topical gel can have problems with blood circulation, including a slow heart rate, low blood pressure, and dizziness. These problems may sometimes be serious and lead to hospitalization. See “What should I tell my doctor before using MIRVASO topical gel?”

• Serious allergic (hypersensitivity) reactionshave happened in people who use MIRVASO topical gel. Stop using MIRVASO topical gel and go to the nearest hospital emergency room right away if you have any of the following signs and symptoms of a serious allergic reaction including:

o swelling of your face, lips, tongue, or throat
o hives
o trouble breathing

The most common side effects of MIRVASO topical gel include:

• redness • flushing • burning sensation of the skin • skin reactions (contact dermatitis).

Skin redness is common after applying MIRVASO topical gel, and may be worse than before you applied it. You may also develop redness on areas of your face that were not affected by rosacea, as well as on your neck and chest.

Skin flushing is common and may happen off and on after applying MIRVASO topical gel. In some cases, the flushing may be new, may happen more often, or you may have increased redness with flushing.

Pale colored skin or very white skin (excessive whitening) can happen at or outside the treated area.

Tell your doctor if you get skin redness, flushing, and pale colored skin that is uncomfortable for you.

These are not all the possible side effects of MIRVASO topical gel.

Call your doctor for medical advice about side effects. You may report side effects to FDA at 1-800-FDA-1088.

General information about the safe and effective use of MIRVASO topical gel
Medicines are sometimes prescribed for purposes other than those listed in a Patient Information leaflet. You can ask your pharmacist or doctor for information about MIRVASO topical gel that is written for health professionals. Do not use MIRVASO topical gel for a condition for which it was not prescribed. Do not give MIRVASO topical gel to other people, even if they have the same symptoms that you have. It may harm them.

What are the ingredients in MIRVASO topical gel?

Active ingredient: brimonidine
Inactive ingredients: carbomer homopolymer type B, glycerin, methylparaben, phenoxyethanol, propylene glycol, purified water, sodium hydroxide, titanium dioxide.

Marketed by: GALDERMA LABORATORIES, L.P., Fort Worth, TX 76177 USA

Made in Canada.

This Patient Information has been approved by the U.S. Food and Drug Administration.
Revised: Nov 2017

Instructions for Use
MIRVASO (Mer-VAY-soe)
(brimonidine) topical geltube

Important:MIRVASO®topical gel is for use on the face only. Do not use MIRVASO topical gel in your eyes, mouth, or vagina.

Keep MIRVASO topical gel out of the reach of children.
If anyone, especially a child, accidentally swallows MIRVASO topical gel, they may have serious side effects and need to be treated in a hospital. Get medical help right away if you, a child, or anyone else swallows MIRVASO topical gel and has any of these symptoms:
• lack of energy, trouble breathing or stops breathing, a slow heart beat, confusion, sweating, restlessness, muscle spasms, or twitching.

Read and follow the steps below so that you use your tube of MIRVASO topical gel correctly:
1. Open the tube of MIRVASO topical gel by gently pressing down on the child resistant cap and twist in the direction of the arrow as shown below (counterclockwise). See Figures A and B. To avoid spilling, do not squeeze the tube while opening or closing.

Figure A

Figure B

2. To apply MIRVASO topical gel to your face, squeeze a pea-sized amount of MIRVASO topical gel from the tube onto your fingertip. See Figure C.

Figure C

3. Apply a pea-sized amount of MIRVASO topical gel onto each of the five areas of your face (forehead, chin,
nose, each cheek) 1 time each day. You will use a total of 5 pea-sized amounts of MIRVASO
topical gel. Spread the gel smoothly and evenly in a thin layer over your face.
Avoid contact with your eyes and lips. Do not apply MIRVASO topical gel to irritated skin or open wounds.

4. To close your MIRVASO topical gel tube, place the cap back on the tube. Gently press down on the child resistant cap and twist to the right (clockwise). See Figure D.

Figure D

5. Wash your hands right away after applying MIRVASO topical gel.

How should I store MIRVASO topical gel?

• Store MIRVASO topical gel at room temperature between 68°F to 77°F (20°C to 25°C).

Keep MIRVASO topical gel and all medicines out of the reach of children.

This Instructions for Use has been approved by the U.S. Food and Drug Administration.

Marketed by: GALDERMA LABORATORIES, L.P.
Fort Worth, TX 76177 USA
Made in Canada.
Revised: October 2015

Instructions for Use
MIRVASO (Mer-VAY-soe)
(brimonidine) topical gel Pump

Important:MIRVASO®topical gel is for use on the face only. Do not use MIRVASO topical gel in your eyes, mouth, or vagina.

Keep MIRVASO topical gel out of the reach of children.

If anyone, especially a child, accidentally swallows MIRVASO topical gel, they may have serious side effects and need to be treated in a hospital. Get medical help right away if you, a child, or anyone else swallows MIRVASO topical gel and has any of these symptoms:

• lack of energy, trouble breathing or stops breathing, a slow heart beat, confusion, sweating, restlessness, muscle spasms, or twitching.

Read and follow the steps below so that you use your MIRVASO topical gel correctly:

1. Push the cap down and turn it counter-clockwise until the cap can be removed. See Figures A and B. The clear sticker will break when opening for the first time.
Note:when the cap is removed, the pump is not child-resistant.

Figure A

Figure B

Figure C

Before the first use, prime the pump by pressing down several times until the medicine is dispensed onto your fingertip.

2. To apply MIRVASO topical gel to your face, dispense a pea-sized amount of MIRVASO topical gel from the pump onto your fingertip. See Figure C.

3. Apply a pea-sized amount of MIRVASO topical gel onto each of the five areas of your face (forehead, chin, nose, each cheek) 1 time each day. You will use a total of 5 pea-sized amounts of MIRVASO topical gel. Spread the gel smoothly and evenly in a thin layer over your face. Avoid contact with your eyes and lips. Do not apply MIRVASO topical gel to irritated skin or open wounds.

4. To close your MIRVASO topical gel pump, place the cap back on the pump. Push down and turn the cap to the right (clockwise) until it stops. This pump is child-resistant again. See Figure D.

Figure D

5. Wash your hands right away after applying MIRVASO topical gel.

How should I store MIRVASO topical gel?

• Store MIRVASO topical gel at room temperature between 68°F to 77°F (20°C to 25°C).

Keep MIRVASO topical gel and all medicines out of the reach of children.

This Instructions for Use has been approved by the U.S. Food and Drug Administration.

Marketed by: GALDERMA LABORATORIES, L.P., Fort Worth, TX 76177 USA,
Made in Canada
Issued: November 2017

PRINCIPAL DISPLAY PANEL 30g Pump Carton

Rx Only
NDC 0299-5980-35

Mirvaso®
(brimonidine) topical gel, 0.33%*
PUMP

*Each gram of Mirvaso topical gel contains 5 mg of brimonidine tartrate, equivalent to 3.3 mg of brimonidine free base

For Topical Use Only
Keep Out of Reach of Children

GALDERMA
NET WT. 30 g

Not for oral, ophthalmic or intravaginal use.
To Open Pump:Push the cap down while turning it counter-clockwise to remove the cap.
Usual Dosage:Apply a pea-size amount once daily to each of the five areas of the face (forehead, chin, nose, and each cheek) avoiding the eyes and lips. See package insert for complete prescribing information.
Each gramcontains the activeingredient brimonidine tartrate 5mg with the inactiveingredients carbomer homopolymer type B, glycerin, methylparaben, phenoxyethanol, propylene glycol, purified water, sodium hydroxide, and titanium dioxide.

Storage:Store at 20° to 25°C (68° to 77°F), excursions permitted between 15° and 30°C (59° and 86°F). [See USP Controlled Room Temperature].

See bottom of carton for lot number and expiration date.
All trademarks are the property of their respective owners.

Marketed by:
GALDERMA LABORATORIES, L.P.
Dallas, TX 75201 USA
Made in Canada
P52848-3